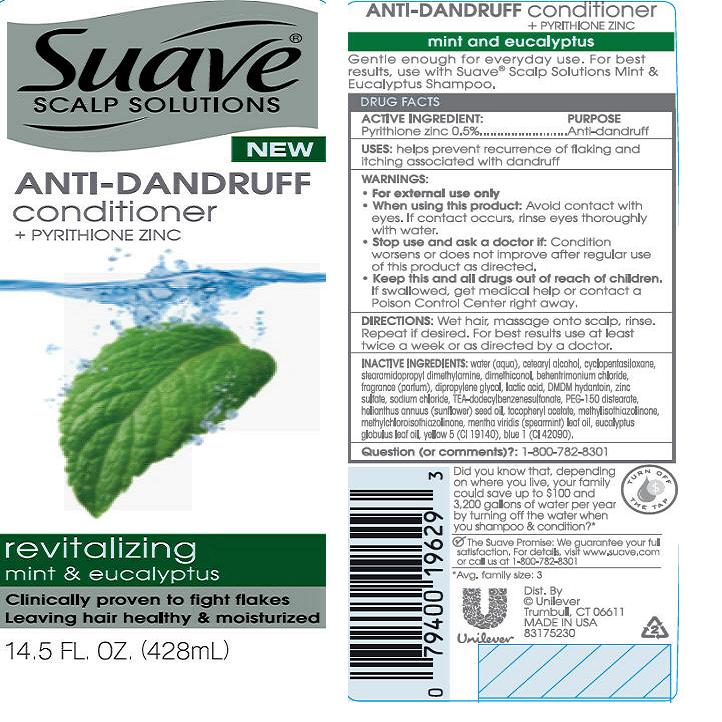 DRUG LABEL: Suave
NDC: 64942-1236 | Form: SUSPENSION
Manufacturer: Conopco Inc. d/b/a Unilever
Category: otc | Type: HUMAN OTC DRUG LABEL
Date: 20120209

ACTIVE INGREDIENTS: Pyrithione Zinc 0.5 mL/100 mL
INACTIVE INGREDIENTS: WATER; CETOSTEARYL ALCOHOL; CYCLOMETHICONE 5; SODIUM CHLORIDE; STEARAMIDOPROPYL DIMETHYLAMINE; BEHENTRIMONIUM CHLORIDE; DMDM HYDANTOIN; TEA-DODECYLBENZENESULFONATE; DIPROPYLENE GLYCOL; LACTIC ACID; ZINC SULFATE; METHYLCHLOROISOTHIAZOLINONE; METHYLISOTHIAZOLINONE; SPEARMINT OIL; PEG-150 DISTEARATE; EUCALYPTUS OIL; FD&C YELLOW NO. 5; FD&C BLUE NO. 1; SUNFLOWER OIL; .ALPHA.-TOCOPHEROL ACETATE, D-; DIMETHICONOL (41 MPA.S)

Suave Revitalizing Mint and Eucalyptus Anti Dandruff Conditioner PDP and drug facts box

Active Ingredient

Pyrithione Zinc (0.5%)

Purpose
Antidandruff

INDICATIONS AND USAGE

Uses: helps prevent recurrence of flaking and itching associated with dandruff

Warnings
For external use only

When using this product: avoid contact with eyes. If contact occurs, rinse eyes thoroughly with water.

Stop use and ask a doctor if: Condition worsens or does not improve after regular use of this product as directed.

KEEP OUT OF REACH OF CHILDREN

Keep this and all drugs out of reach of children. If swallowed, get medical help or contact a Poison Control Center right away.

DOSAGE AND ADMINISTRATION

Directions: Wet hair, massage onto scalp, rinse. Repeat if desired. For best results use at least twice a week or as directed by a doctor.

Inactive Ingredients
Water (Aqua)
Cetearyl Alcohol
Cyclopentasiloxane
Stearamidopropyl Dimethylamine
Dimethiconol
Behentrimonium Chloride
Fragrance (Parfum)
Dipropylene Glycol
Lactic Acid
DMDM Hydantoin
Zinc Sulfate
Sodium Chloride
TEA-Dodecylbenzenesulfonate
PEG-150 Distearate
Helianthus Annuus (Sunflower) Seed Oil
Tocopheryl Acetate
Methylisothiazolinone
Methylchloroisothiazolinone
Mentha Viridis (Spearmint) Leaf Oil
Eucalyptus Globulus Leaf Oil
Yellow 5 (CI 19140)
Blue 1 (CI 42090)

QUESTIONS

Question (or comments)?: 1-800-782-8301

PACKAGE LABEL

PDP